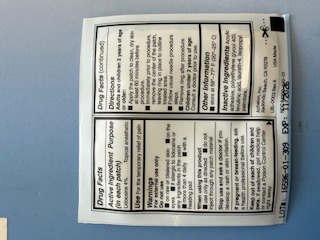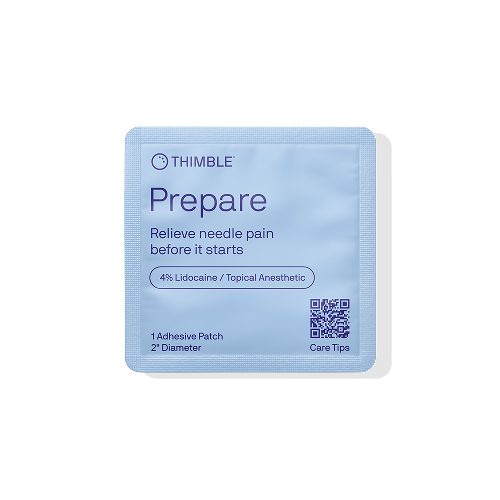 DRUG LABEL: Achelon Lidocaine Patch
NDC: 84209-400 | Form: PATCH
Manufacturer: Achelon, Inc
Category: otc | Type: HUMAN OTC DRUG LABEL
Date: 20250326

ACTIVE INGREDIENTS: LIDOCAINE 7.54 mg/60.81 cm2
INACTIVE INGREDIENTS: LEVULINIC ACID; POLYETHYLENE GLYCOL 400; ACRYLIC ACID/ETHYLENE COPOLYMER (600 MPA.S); ISOPROPYL PALMITATE

Achelon Lidocaine 4% Patch; 1 Patch per Pouch

Active Ingredients

Lidocaine 4%

Purpose

Topical Analgesic

Uses

For the temporary relief of pain.

Warnings

For external use only.

Do not use

- on raw or blistered skin
- on the eyes
- if alergic to lidocaine or any ingredient in the patch
- more than 4 daily
- with a heating pad

When using this product

- Use only as directed
- Do not inject through any patch material

Stop use or ask a doctor if

If you develop a rash or skin irritation

If pregnant or breast feeding

ask a health professional before use.

Keep out of reach of children and pets

If swallowed get medical help or contact a Poison Control Center right away

Directions

Adults and children 2 years of age or older:

- Apply the patch to clean dry skin 60 minutes before procedure
- Immediately prior to procedure, remove the center of the patch, leaving ring in place to outline treated area
- Follow usual needle procedure steps
- Remove ring after procedure

Children under 2 years of age:

Consult a doctor prior to use

Other information

- store at 68o - 77o F (20o - 25o C)

Inactive Ingredients

Acrylic adhesive, Polyethylene film, Mylar release liner, Polyethylene Glycol, Levulinic acid, BrijL4LQ, Isopropyl Palmitate